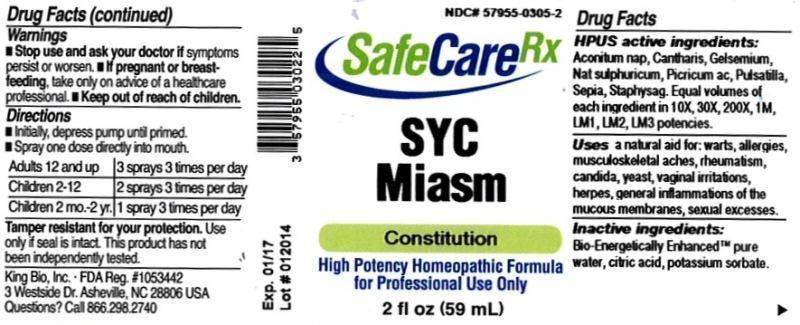 DRUG LABEL: SYC Miasm
NDC: 57955-0305 | Form: LIQUID
Manufacturer: King Bio Inc.
Category: homeopathic | Type: HUMAN OTC DRUG LABEL
Date: 20140203

ACTIVE INGREDIENTS: ACONITUM NAPELLUS 10 [hp_X]/59 mL; LYTTA VESICATORIA 10 [hp_X]/59 mL; GELSEMIUM SEMPERVIRENS ROOT 10 [hp_X]/59 mL; SODIUM SULFATE 10 [hp_X]/59 mL; PICRIC ACID 10 [hp_X]/59 mL; PULSATILLA VULGARIS 10 [hp_X]/59 mL; SEPIA OFFICINALIS JUICE 10 [hp_X]/59 mL; DELPHINIUM STAPHISAGRIA SEED 10 [hp_X]/59 mL
INACTIVE INGREDIENTS: WATER; CITRIC ACID MONOHYDRATE; POTASSIUM SORBATE

SYC Miasm™

ACTIVE INGREDIENT

Drug Facts__________________________________________________________________________________________________________

HPUS active ingredients: Aconitum napellus, Cantharis, Gelsemium sempervirens, Natrum sulphuricum, Picricum acidum, Pulsatilla, Sepia, Staphysagria. Equal volumes of each ingredient in 10X, 30X, 200X, 1M, LM1, LM2, LM3 potencies.

INDICATIONS AND USAGE

Uses a natural aid for: warts, allergies musculoskeletal aches, rheumatism, candida, yeast, vaginal irritations, herpes, general inflammations of the mucous membranes, sexual excesses.

Inactive Ingredients:

Bio-Energetically Enhanced™ pure water, citric acid and potassium sorbate.

Warnings

- Stop use and ask a doctor, if symptoms persist or worsen.

- If pregnant or breast-feeding, take only on advice of a healthcare professional.

- Keep out of reach of children

DOSAGE AND ADMINISTRATION

- Initially, depress pump until primed.
- Spray one dose directly into mouth.
- Adults 12 and up - 3 sprays 3 times per day.
- Children 2-12 - 2 sprays 3 times per day.
- Children 2 mo. - 1 spray 3 times per day

OTHER SAFETY INFORMATION

Tamper resistant for your protection. Use only if safety seal is intact. This product has not been independently tested.

PURPOSE

Uses a natural aid for:

- warts
- allergies
- musculoskeletal aches
- rheumatism
- candida
- yeast
- vaginal irritations
- herpes
- general inflammations of the mucous membranes
- sexual excesses